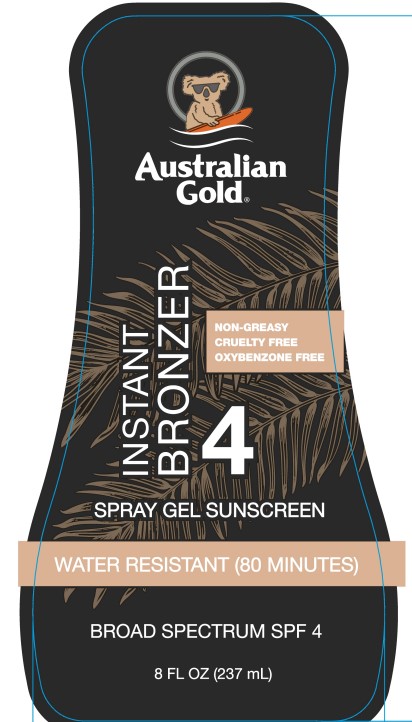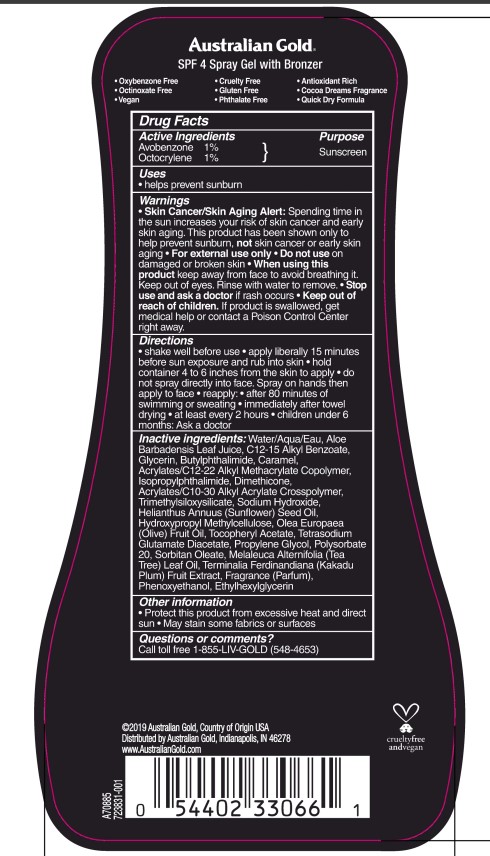 DRUG LABEL: Australian Gold
NDC: 13630-0236 | Form: SPRAY
Manufacturer: Prime Packaging, Inc.
Category: otc | Type: HUMAN OTC DRUG LABEL
Date: 20220429

ACTIVE INGREDIENTS: AVOBENZONE 9.71 mg/1 mL; OCTOCRYLENE 9.71 mg/1 mL
INACTIVE INGREDIENTS: DIMETHICONE; CARBOMER INTERPOLYMER TYPE A (55000 CPS); OLIVE OIL; TETRASODIUM GLUTAMATE DIACETATE; TEA TREE OIL; KAKADU PLUM; N-BUTYLPHTHALIMIDE; CARAMEL; ISOPROPYLPHTHALIMIDE; TRIMETHYLSILOXYSILICATE (M/Q 0.6-0.8); SUNFLOWER OIL; POLYSORBATE 20; WATER; ALOE VERA LEAF; ALKYL (C12-15) BENZOATE; GLYCERIN; SODIUM HYDROXIDE; HYPROMELLOSES; .ALPHA.-TOCOPHEROL ACETATE; ETHYLHEXYLGLYCERIN; PROPYLENE GLYCOL; SORBITAN MONOOLEATE

Australian Gold Instant Bronzer Spray Gel Sunscreen Broad Spectrum SPF 4

Active Ingredients

Avobenzone 1%

Octocrylene 1%

Purpose

Sunscreen

Uses

- helps prevent sunburn

Warnings

Skin Cancer/Skin Aging Alert: Spending time in the sun increases your risk of skin cancer and early skin aging. This product has been shown only to prevent sunburn, not skin cancer or early skin aging.

OTHER SAFETY INFORMATION

For external use only

Do not use on damaged or broken skin.

When using this product keep away from face to avoid breathing it. Keep out of eyes. Rinse with water to remove.

Stop use and ask a doctor if rash occurs

Keep out of reach of children. If product is swallowed, get medical help or contact a Poison Control Center right away.

Directions

- shake well before use
- apply liberally 15 minutes before sun exposure and rub into skin
- hold container 4 to 6 inches from the skin to apply
- do not spray directly into face. Spray on hands then apply to face
- reapply:
- after 80 minutes of swimming or sweating
- immediately after towel drying
- at least every 2 hours
- children under 6 months: Ask a doctor

Inactive Ingredients

Water, Aloe Barbadensis Leaf Juice, C12-15 Alkyl Benzoate, Glycerin, Butylphthalimide, Caramel, Phenoxyethanol, Fragrance, Acrylates/C12-22 Alkyl Methacrylate Copolymer, Isopropylphthalimide, Dimethicone, Acrylates/C10-30 Alkyl Acrylate Crosspolymer, Polysorbate 20, Trimethylsiloxysilicate, Sodium Hydroxide, Helianthus Annuus (Sunflower) Seed Oil, Hydroxypropyl Methylcellulose, Olea Europaea (Olive) Fruit Oil, Tocopheryl Acetate, Tetrasodium Glutamate Diacetate, Ethylhexylglycerin, Propylene Glycol, Sorbitan Oleate, Melaleuca Alternifolia (Tea Tree) Leaf Oil, Terminalia Ferdinandiana (Kakadu Plum) Fruit Extract

Other information

- Protect this product from excesive heat and direct sun
- May stain some fabrics or surfaces

Questions or Comments?

Call toll free 1-855-LIV-GOLD (548-4653)